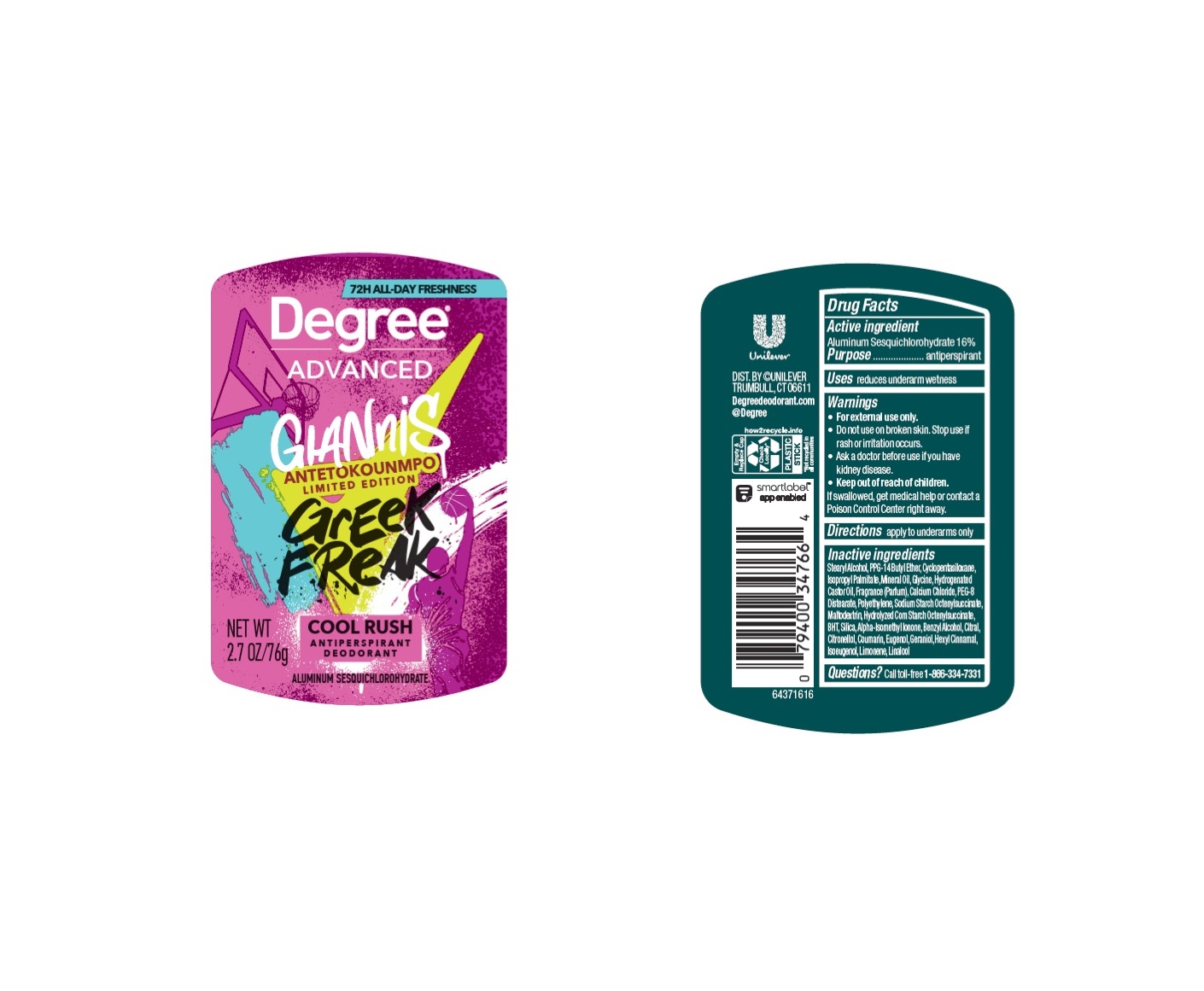 DRUG LABEL: Degree
NDC: 64942-2318 | Form: STICK
Manufacturer: Conopco Inc. d/b/a/ Unilever
Category: otc | Type: HUMAN OTC DRUG LABEL
Date: 20240621

ACTIVE INGREDIENTS: ALUMINUM SESQUICHLOROHYDRATE 16 g/100 g
INACTIVE INGREDIENTS: ISOPROPYL PALMITATE; GERANIOL; CITRAL; MINERAL OIL; HIGH DENSITY POLYETHYLENE; CALCIUM CHLORIDE; GLYCINE; HYDROGENATED CASTOR OIL; CYCLOMETHICONE 5; BUTYLATED HYDROXYTOLUENE; MALTODEXTRIN; PEG-8 DISTEARATE; SILICON DIOXIDE; PPG-14 BUTYL ETHER; STEARYL ALCOHOL; LIMONENE, (+)-; LINALOOL, (+/-)-; COUMARIN; .ALPHA.-HEXYLCINNAMALDEHYDE; .BETA.-CITRONELLOL, (R)-; ISOMETHYL-.ALPHA.-IONONE; BENZYL ALCOHOL; EUGENOL; ISOEUGENOL

Degree Advanced Greek Freak Cool Rush Antiperspirant Deodorant

Drug Facts

Active ingredient

Aluminum Sesquichlorohydrate (16%)

Purpose

antiperspirant

Uses

reduces underarm wetness

Warnings

• For external use only.
• Do not use on broken skin .
• Ask a doctor before use if you have kidney disease.
• Stop use if rash or irritation occurs.

• Keep out of reach of children.

If swallowed, get medical help or contact a Poison Control Center right away.

Directions

apply to underarms only

Inactive ingredients

Stearyl Alcohol, PPG-14 Butyl Ether, Cyclopentasiloxane, Isopropyl Palmitate, Mineral Oil, Glycine, Hydrogenated Castor Oil, Fragrance (Parfum), Calcium Chloride, PEG-8 Distearate, Polyethylene, Sodium Starch Octenylsuccinate, Maltodextrin, Hydrolyzed Corn Starch Octenylsuccinate, BHT, Silica, Alpha-Isomethyl Ionone, Benzyl Alcohol, Citral, Citronellol, Coumarin, Eugenol, Geraniol, Hexyl Cinnamal, Isoeugenol, Limonene, Linalool

Questions?

Call toll-free 1-866-334-7331